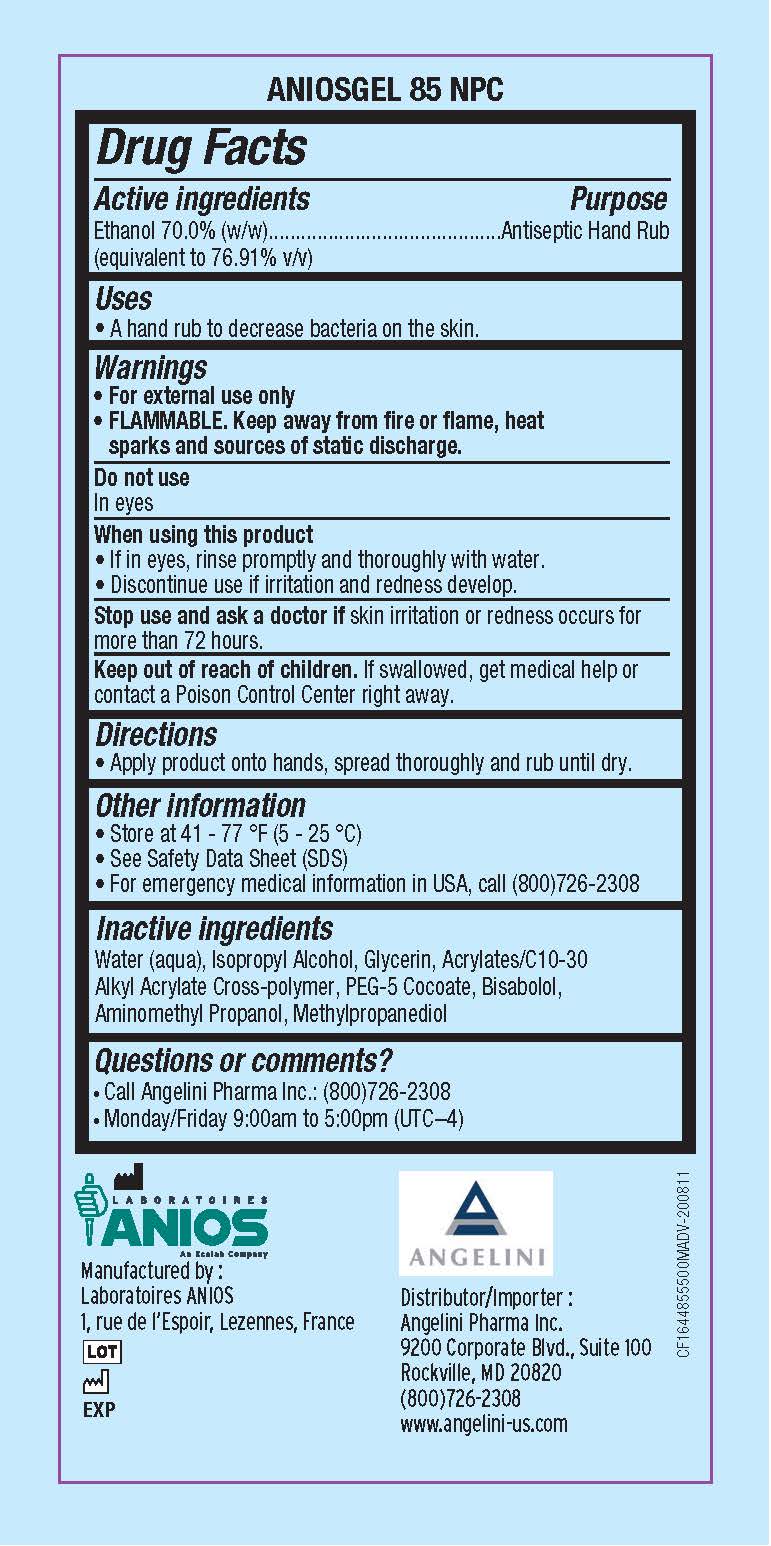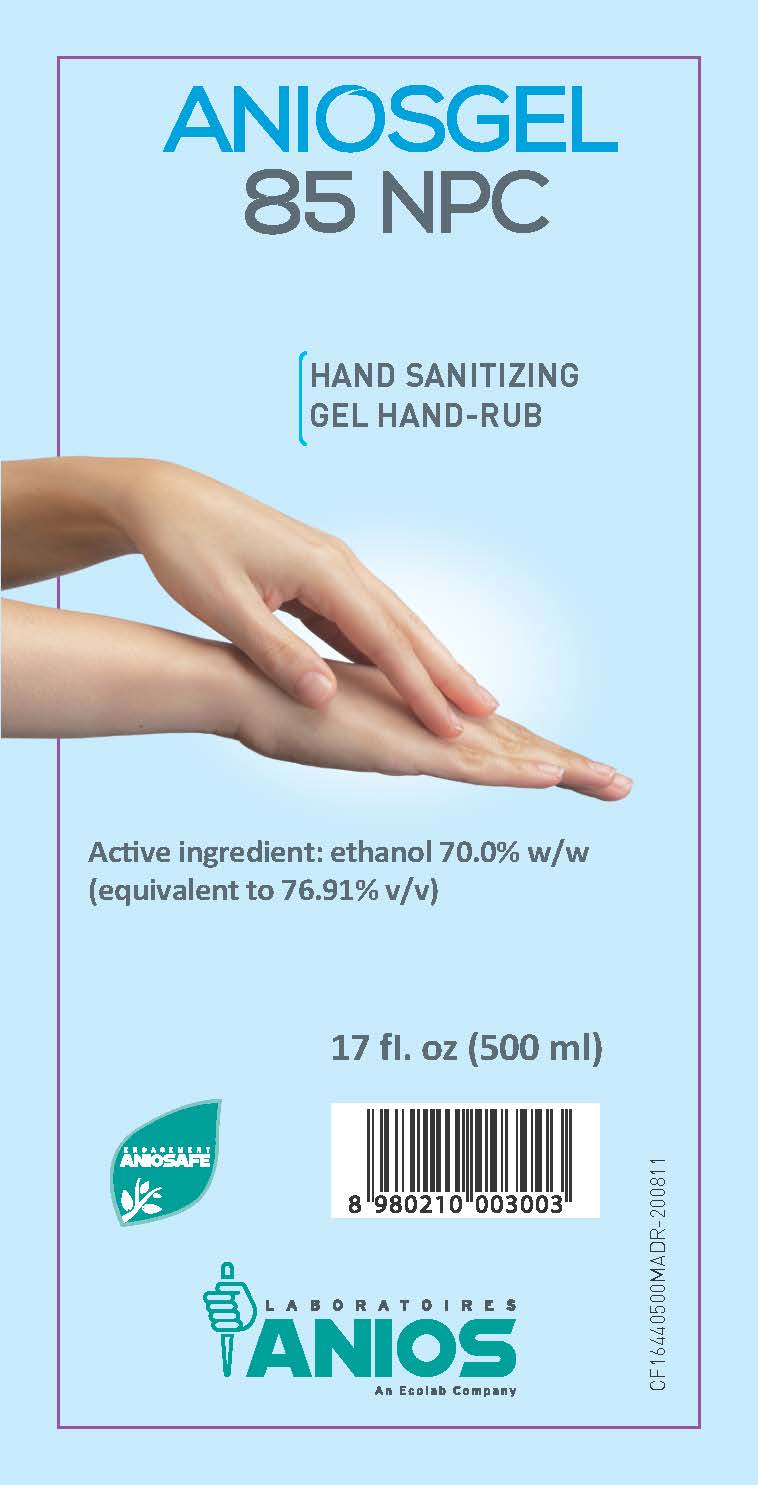 DRUG LABEL: ANIOSGEL 85
NDC: 62169-203 | Form: GEL
Manufacturer: Laboratoires Anios
Category: otc | Type: HUMAN OTC DRUG LABEL
Date: 20250211

ACTIVE INGREDIENTS: ALCOHOL 377.5 mL/500 mL
INACTIVE INGREDIENTS: ISOPROPYL ALCOHOL; GLYCERIN; ACRYLATES/C10-30 ALKYL ACRYLATE CROSSPOLYMER (60000 MPA.S); DIETHYLAMINOETHYL PEG-5 COCOATE; LEVOMENOL; AMINOMETHYLPROPANOL; METHYLPROPANEDIOL

ACTIVE INGREDIENT

Ethanol 70.0% (w/w) (equivalent to 76.91% v/v)

PURPOSE

Antiseptic Hand Rub

Uses

A hand rub to decrease bacteria on the skin.

Warnings

- For external use only
- FLAMMABLE. Keep away from fire or flame, heat sparks and sources of static discharge.

Do not use

In eyes

When using this product

- If in eyes, rinse promptly and thoroughly with water.
- Discontinue use if irritation and redness develop.

Stop use and ask a doctor if skin irritatin or redness occurs for more than 72 hours.

Keep out of reach of children. If swallowed, get medical help or contact a poison Control Center right away.

DOSAGE AND ADMINISTRATION

Apply product onto hands, spread thoroughly and rub until dry.

Other information

- Store at 41 - 77 °F (5 - 25 °C)
- See Safety Data Sheet (SDS)
- For emergency medical information in USA, call (800)726-2308

INACTIVE INGREDIENT

Inactive ingredients Water (aqua), Isopropyl Alcohol, Glycerin, Acrylates/C10-30 Alkyl Acrylate Cross-polymer, PEG-5 Cocoate, Bisabolol, Aminomethyl Propanol, Methylpropanediol

Questions or comments? Call (800)726-2308 Monday/Friday 9:00am to 5:00pm (UTC-4)

Principal display panel and representative label

ANIOSGEL

85 NPC

HAND SANITIZING

GEL HAND-RUB

Active ingredient: ethanol 70.0% w/w (equivalent to 76.91% v/v)

17 fl oz (500 mL)

Manu factured by:

Laboratoires Anios and Ecolab Company

1, rue de l'Espoir, Lezennes, France